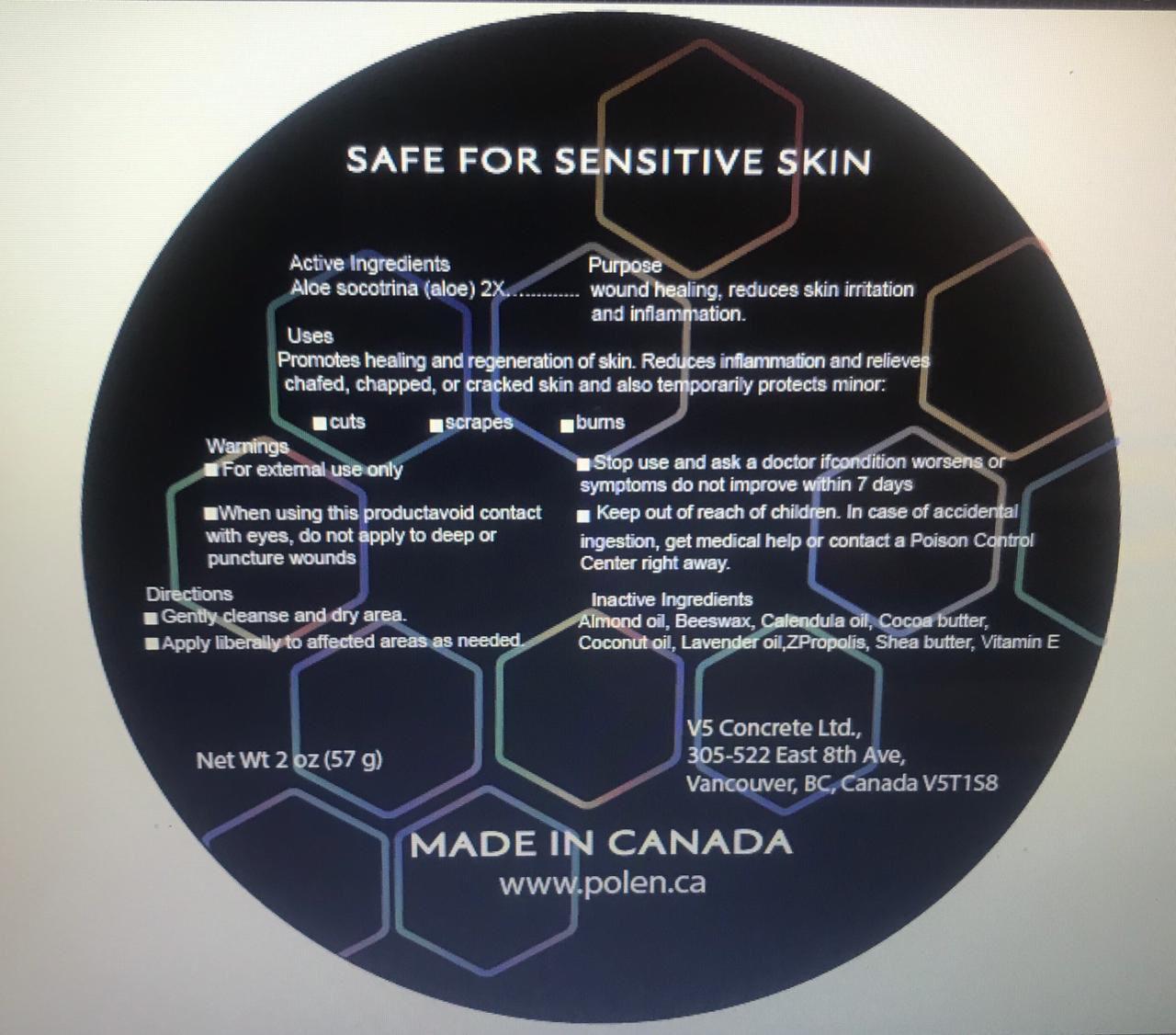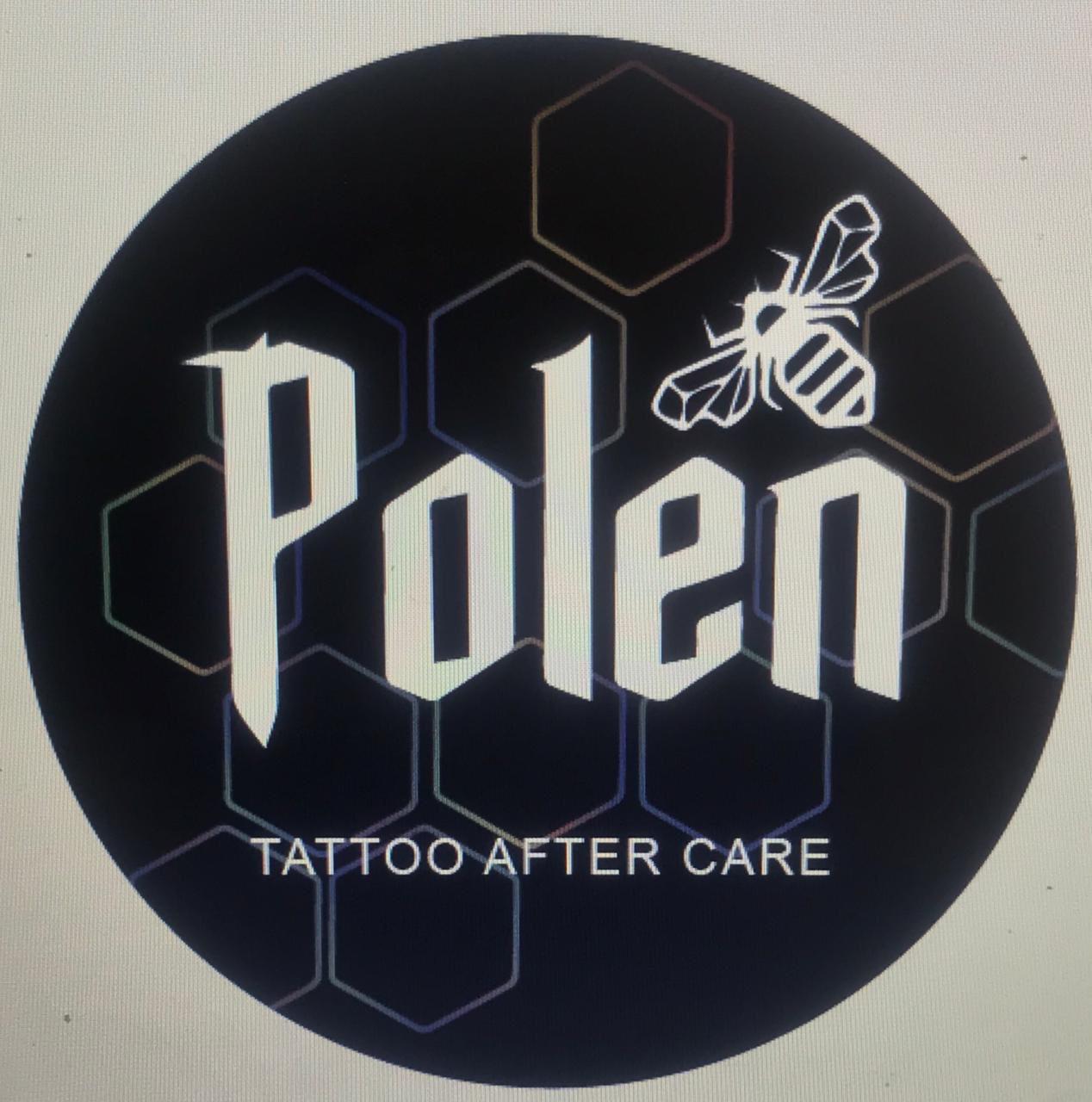 DRUG LABEL: Polen Natural After Care
NDC: 81859-001 | Form: OINTMENT
Manufacturer: V5 Concrete Ltd.
Category: homeopathic | Type: HUMAN OTC DRUG LABEL
Date: 20210506

ACTIVE INGREDIENTS: ALOE 2 [hp_X]/57 g
INACTIVE INGREDIENTS: PROPOLIS WAX; .ALPHA.-TOCOPHEROL; LAVENDER OIL; CALENDULA OFFICINALIS SEED OIL; COCONUT OIL; SHEA BUTTER; YELLOW WAX; COCOA BUTTER; ALMOND OIL

Polen Natural After Care Skin Cream

ACTIVE INGREDIENT

Aloe socotrina (aloe) 2X

Purpose

Wound healing

Uses

Helps reduce inflammation, promotes healing and regeneration of skin, and enhances the colors in your tattoos.

WARNINGS

For external use only.

WHEN USING

Avoid contact with eyes, do not apply to deep or puncture wounds.

Stop use and ask a doctor if condition worsens or symptoms do not improve within 7 days.

Keep out of reach of children. In case of accidental ingestion, get medical help or contact a Poison Control Center right away.

Directions

Gently cleanse and dry area. Apply liberally to affected areas as needed.

INACTIVE INGREDIENT

Almond oil, Beeswax, Calendula oil, Cocoa butter, Coconut oil, Lavender oil, Propolis, Shea butter, Vitamin E

PACKAGE LABEL

NDC: 81859-001-02